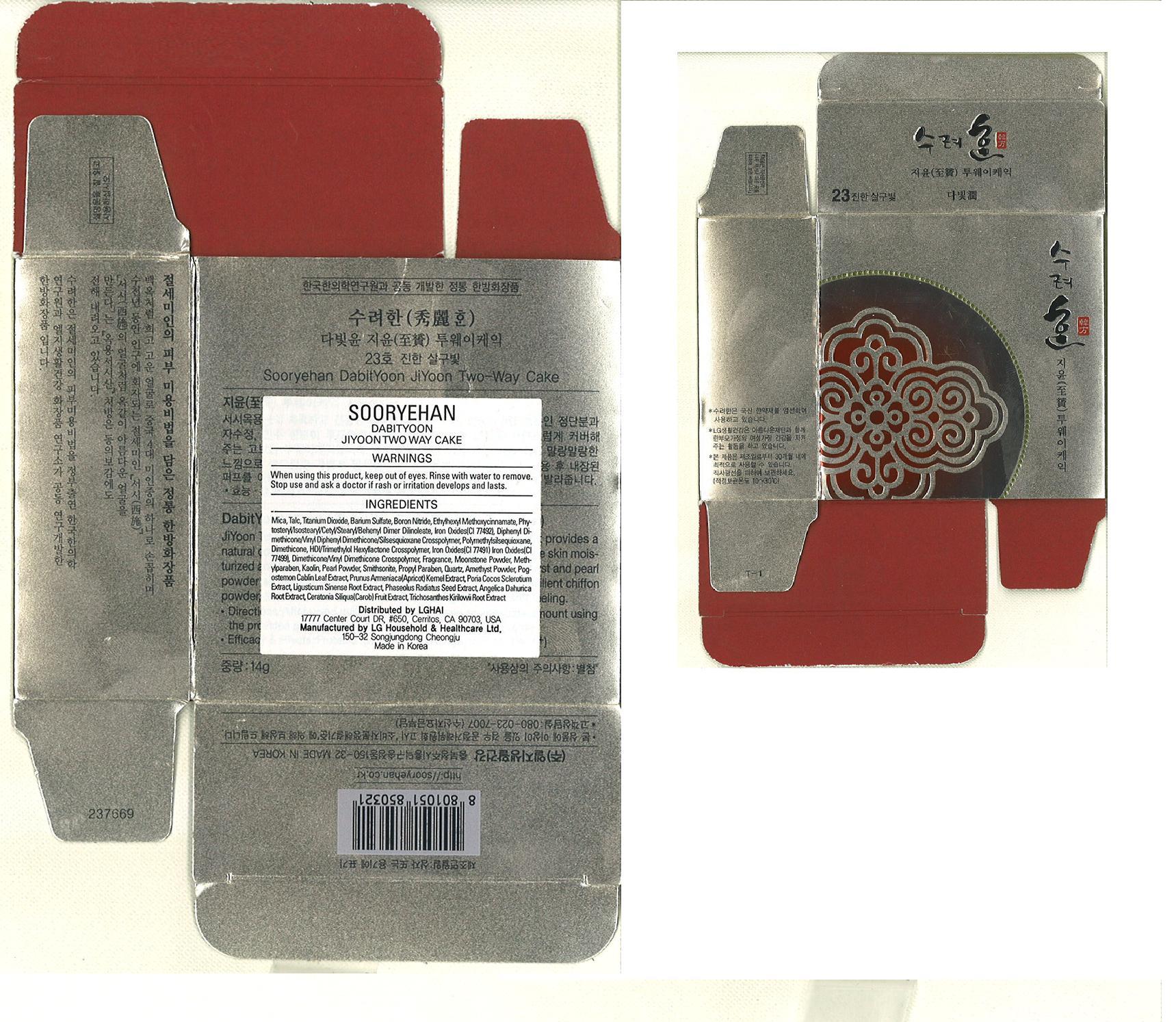 DRUG LABEL: Sooryehan Dabityoon Jiyoon Two way cake 23 
NDC: 53208-418 | Form: POWDER
Manufacturer: LG Household and Healthcare, Inc.
Category: otc | Type: HUMAN OTC DRUG LABEL
Date: 20100330

ACTIVE INGREDIENTS: OCTINOXATE 3.5 g/100 g; Titanium Dioxide 14.00 g/100 g
INACTIVE INGREDIENTS: Talc; Barium Sulfate; FERRIC OXIDE YELLOW; FERRIC OXIDE RED; FERROSOFERRIC OXIDE; Methylparaben; Kaolin; PROPYLPARABEN; PERSIC OIL; AMERICAN GINSENG; CAROB

Drug Facts

ACTIVE INGREDIENT

TITANIUM DIOXIDE 14g/100g

OCTINOXATE 3.5g/100g

WARNINGS AND PRECAUTIONS

For external use only

Keep out of reach of children. Is swallowed, get medical help or contact a Poison Control Center right away.

WHEN USING

Keep out of eyes. Rinse with water to remove.

Stop use if a rash or irritation develops and lasts.

PACKAGE LABEL

SooRyeHan

DabitYoon

Jiyoon

Two Way Cake 23